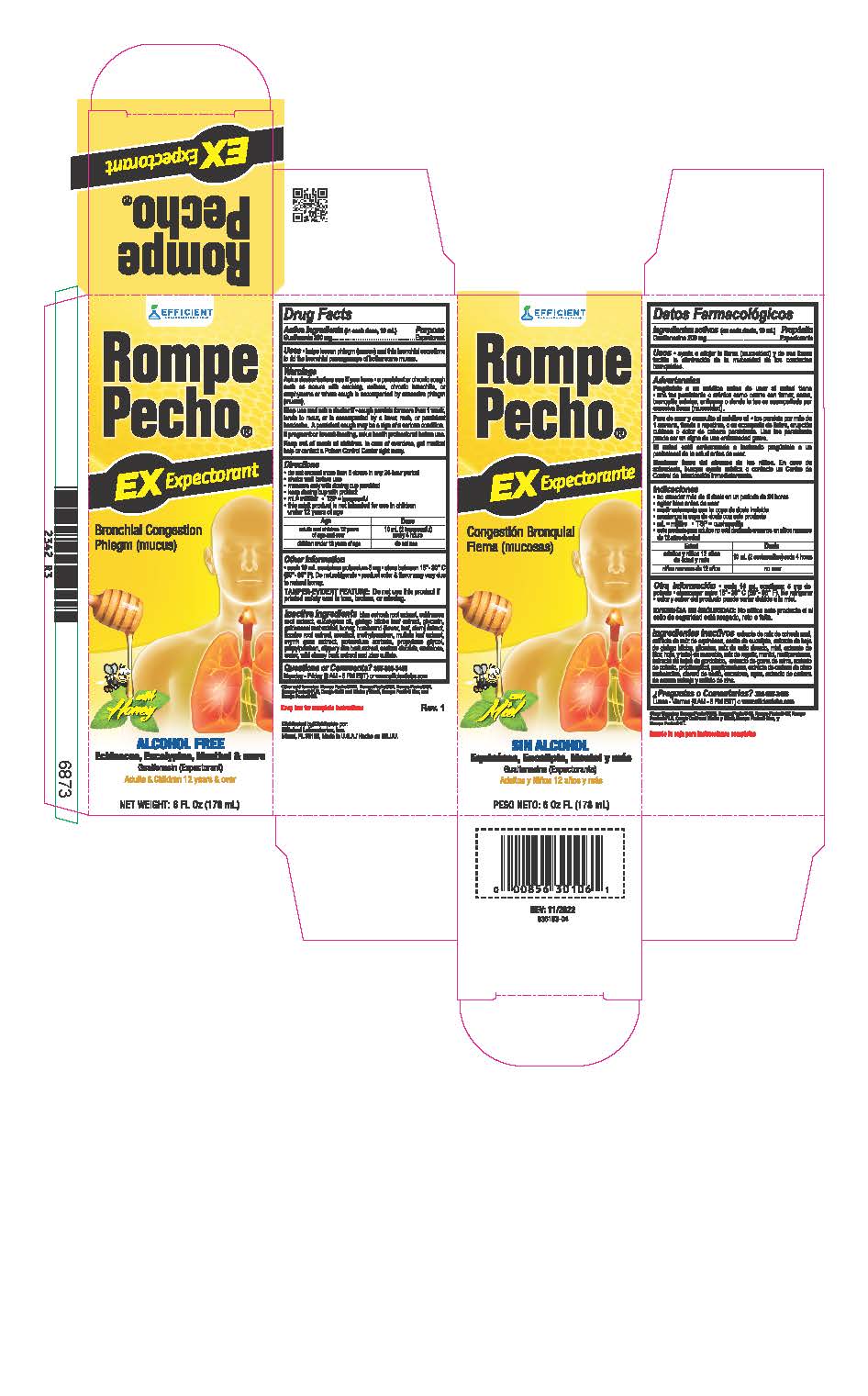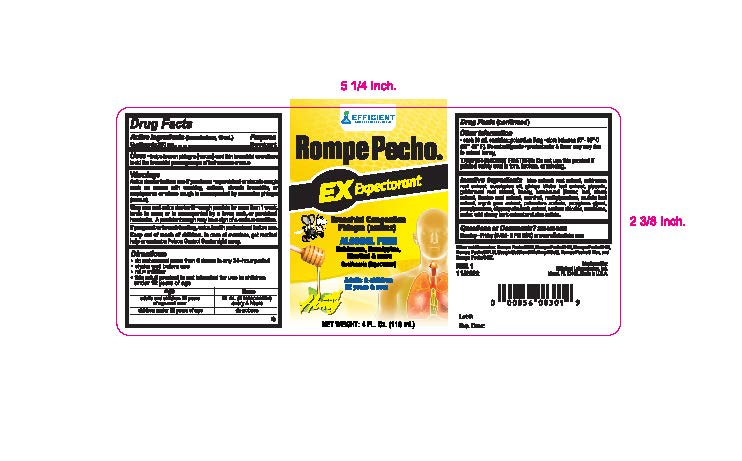 DRUG LABEL: Rompe Pecho
NDC: 58593-829 | Form: LIQUID
Manufacturer: Efficient Laboratories Inc
Category: otc | Type: HUMAN OTC DRUG LABEL
Date: 20241114

ACTIVE INGREDIENTS: GUAIFENESIN 200 mg/10 mL
INACTIVE INGREDIENTS: GLYCERIN; SUCRALOSE; CAULOPHYLLUM THALICTROIDES ROOT; ECHINACEA, UNSPECIFIED; EUCALYPTUS GLOBULUS LEAF; GINKGO; GOLDENSEAL; HONEY; GLYCYRRHIZA GLABRA; MENTHOL; METHYLPARABEN; VERBASCUM DENSIFLORUM LEAF; MYRRH; ASCLEPIAS TUBEROSA ROOT; POTASSIUM SORBATE; PROPYLENE GLYCOL; PROPYLPARABEN; WATER; ULMUS RUBRA BARK; SODIUM CHLORIDE; PRUNUS SEROTINA BARK; ZINC SULFATE; HOREHOUND

Drug Facts

Active Ingredients:(in each teaspoonful 5 ml.) Purpose

Guaifenesin 200 mg ................................................................... Expectorant

Purpose

Expectorant

Uses:

- Helps loosen phlegm (mucus) and thin bronchial secretions to rid bronchial passageways of bothersome mucus.

Warnings

Do not exceed recommended dosage.

Ask a doctor before use if you have

- a persistent or chronic cough such as occurs with smoking, asthma, chronic bronchitis, or emphysema or where cough is accompanied by excessive phlegm (mucus)

Stop use and ask a doctor if

- cough persists for more than 1 week, tends to recur, or is accompanied by a fever, rash, or persistent headache. A persistent cough may be a sign of a serious condition.

PREGNANCY OR BREAST FEEDING

If pregnant or breast-feeding,ask a health professional before use.

Keep out of reach of children.

In case of overdose, get medical help or contact a Poison Control Center right away.

Directions

- do not exceed more than 6 doses in any 24 hour period
- mL=milliliter
- this adult product is not intended for use in children under 12 years

Age | Dose
adults and children 12 years and over | 10 mL (2 teaspoonful) every 4 hours
children under 12 years of age | do not use

Other information

- each 10 mL contains: potassium 5 mg
- store between 15° - 30°C (59° - 86°F). Do not refrigerate
- product color & flavor may vary due to natural honey

TAMPER - EVIDENT FEATURE: Do not use this product if printed safety seal over cap is torn, broken or missing.

Inactive Ingredients:

Blue Cohosh root extract, Echinacea root extract, Eucalyptus Oil, Ginkgo Biloba leaf extract, glycerin, Golden Seal Root extract,
Honey, Horehound (flower, leaf, stem) extract, Licorice Root extract, Menthol, Methylparaben, Mullein leaf extract, Myrrh gum extract, Potassium Sorbate, Propylene glycol, Propylparaben, Slippery Elm Bark extract, Sodium Chloride,Sucralose, Water, Wild cherry bark extract and Zinc Sulfate.

Questions or Comments? 305-805-3456

Monday - Friday (9AM to 5PM EST) or www.efficientlabs.com